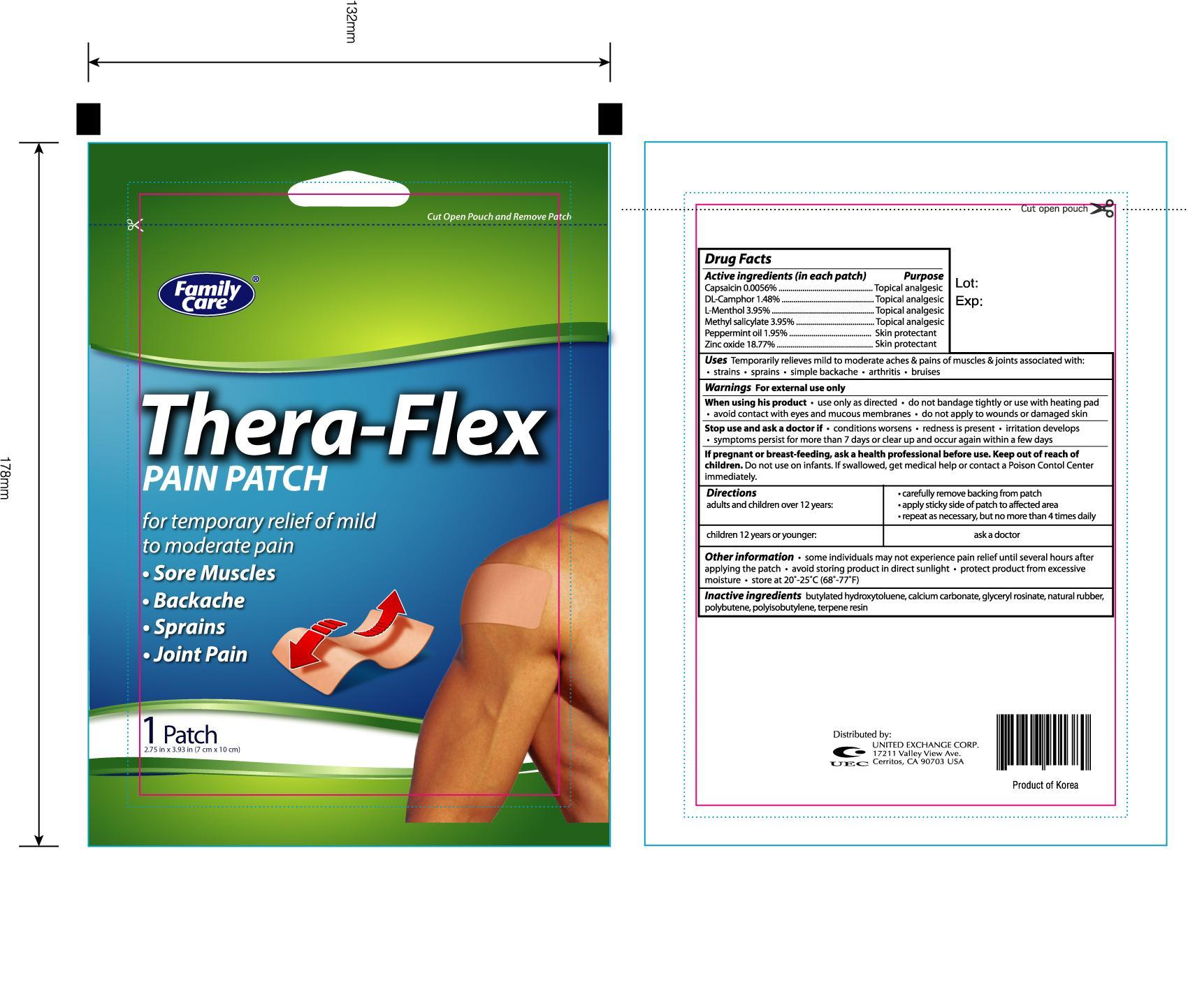 DRUG LABEL: FAMILY CARE THERA FLEX PAIN 
NDC: 65923-100 | Form: PATCH
Manufacturer: UNITED EXCHANGE CORP
Category: otc | Type: HUMAN OTC DRUG LABEL
Date: 20120930

ACTIVE INGREDIENTS: CAPSAICIN 0.0056 g/1 1; CAMPHOR (SYNTHETIC) 1.48 g/1 1; MENTHOL 3.95 g/1 1; METHYL SALICYLATE 3.95 g/1 1; PEPPERMINT OIL 1.95 g/1 1; ZINC OXIDE 18.77 g/1 1
INACTIVE INGREDIENTS: BUTYLATED HYDROXYTOLUENE; CALCIUM CARBONATE; NATURAL LATEX RUBBER

Drug Facts

Active ingredients (in each patch) Purpose

Capsaicin 0.0056%...............................................................................................................Topical analgesic

DL-Camphor 1.48%...............................................................................................................Topical analgesic

L-Menthol 3.95%...................................................................................................................Topical analgesic

Methyl salicylate 3.95%.........................................................................................................Topical analgesic

Peppermint oil 1.95%.............................................................................................................Skin protectant

Zinc oxide 18.77%.................................................................................................................Skin protectant

Uses

Temporarily relieves mild to moderate aches and pains of muscles and joints associated with:

- strains
- sprains
- simple backache
- arthritis
- bruises

Warnings For external use only

When using this product

- use only as directed
- do not bandage tightly or use with heating pad
- avoid contact with eyes and mucous membranes
- do not apply to wounds or damaged skin

Stop use and ask a doctor if

- conditions worsens
- redness is present
- irritation develops
- symptoms persist for more than 7 days or clear up and occur again within a few days

PREGNANCY OR BREAST FEEDING

If pregnant or breast feeding, ask a health professional before use.

Keep out of reach of children.

Do not use on infants. If swallowed, get medical help or contact a Poison Control Center immediately.

Directions

adults and children over 12 years:

- carefully remove backing from patch
- apply sticky side of patch to affected area
- repeat as necessary, but no more than 4 times daily

children 12 years or younger:

- ask a doctor

Other information

- some individuals may not experience pain relief until several hours after applying the patch
- avoid storing product in direct sunlight
- protect product from excessive moisture
- store at 20o-25oC (68o-77oF)

Inactive ingredients

butylated hydroxytoluene, calcium carbonate, glyceryl rosinate, natural rubber, polybutene, polyisobutylene, terpene resin

DOSAGE AND ADMINISTRATION

Distributed by:

UNITED EXCHANGE CORP.

17211 Valley View Ave.

Cerritos, CA 90703 USA

Made in Korea